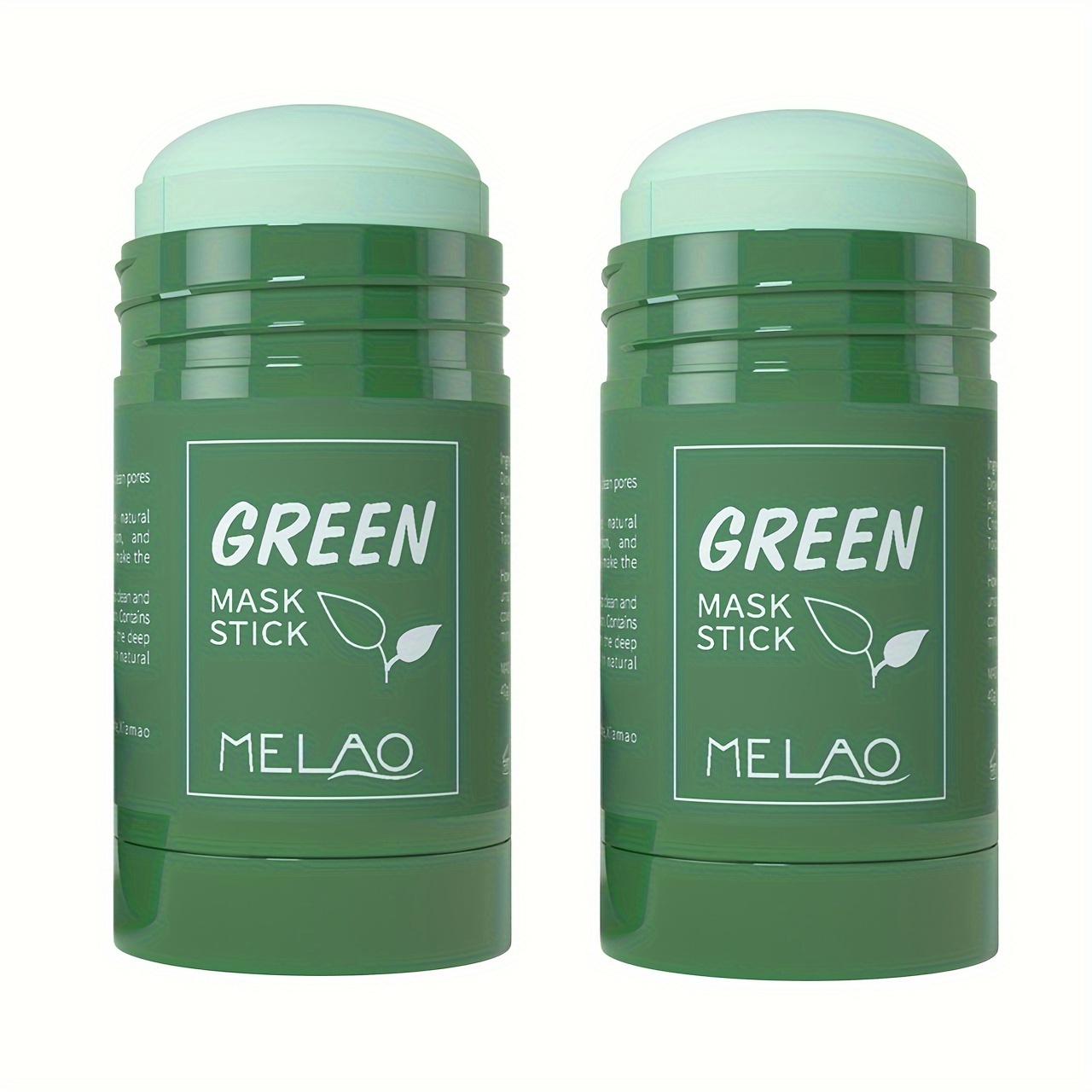 DRUG LABEL: MELAO Green Mask Stick
NDC: 83566-576 | Form: STICK
Manufacturer: Guangzhou Yilong Cosmetics Co., Ltd
Category: otc | Type: HUMAN OTC DRUG LABEL
Date: 20240809

ACTIVE INGREDIENTS: GELLAN GUM (LOW ACYL) 0.5 g/100 g; SALICYLIC ACID 1 g/100 g
INACTIVE INGREDIENTS: DIPROPYLENE GLYCOL 7 g/100 g; HELIANTHUS ANNUUS WHOLE 2.3 g/100 g; WATER 55 g/100 g; COCAMIDOPROPYL DIMETHYLAMINE 0.93 g/100 g; DISTEARDIMONIUM HECTORITE 0.3 g/100 g; ISOSTEARIC ACID 5 g/100 g; SODIUM STEARATE 4 g/100 g; SODIUM HYDROXIDE 0.57 g/100 g; ETHYLHEXYLGLYCERIN 0.2 g/100 g; SACCHAROMYCES CEREVISIAE 2.4 g/100 g; OPUNTIA FICUS-INDICA SEED OIL 2 g/100 g; PHENOXYETHANOL 0.5 g/100 g; KAOLIN 6 g/100 g; HAMAMELIS VIRGINIANA FLOWER WATER 3.6 g/100 g; GLYCERIN 5 g/100 g; ALOE FEROX LEAF 3.7 g/100 g

MELAO Green Mask Stick 40g

Active ingredients

Salicylic Acid 1%

Gellan Gum 0.50%

Inactive ingredients

Water 55%

Propylene Glycol 7%

Kaolin 6%

Glycerin 5%

Stearic Acid 5%

Aloe Barbadensis Leaf Juice 3.70%

Hamamelis Virginiana (Witch Hazel) Water 3.60%

Saccharomyces/Xylinum/Black Tea Ferment 2.40%

Helianthus Annuus (Sunflower) Seed Oil 2.30%

Opuntia Ficus-Indica Seed Oil 2%

Sodium Stearate 4%

Cocamidopropyl Dimethylamine 0.93%

Sodium Hydroxide 0.57%

Phenoxyethanol 0.50%

Disteardimonium Hectorite 0.30%

Ethylhexylglycerin 0.20%

Purpose

Moisture

Uses

STEP1: Clean and thoroughly dry your skin.

STEP2: Twist the bottom of the product.

STEP3: Gently apply to the skin or other desired areas.

Warning

.For external use only.

Stop use and ask a doctor if

rash occurs.

Do not use

on damaged or broken skin.

When using this product

keep out of eyes. Rinse withwater to remove.

Keep out of reach of children.

If swallowed, get medical help or contact a Poison Control Center right away.

DOSAGE & ADMINISTRATION

If swallowed, get medical help or contact a Poison Control Center right away.